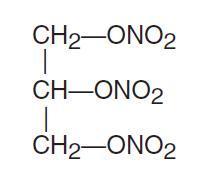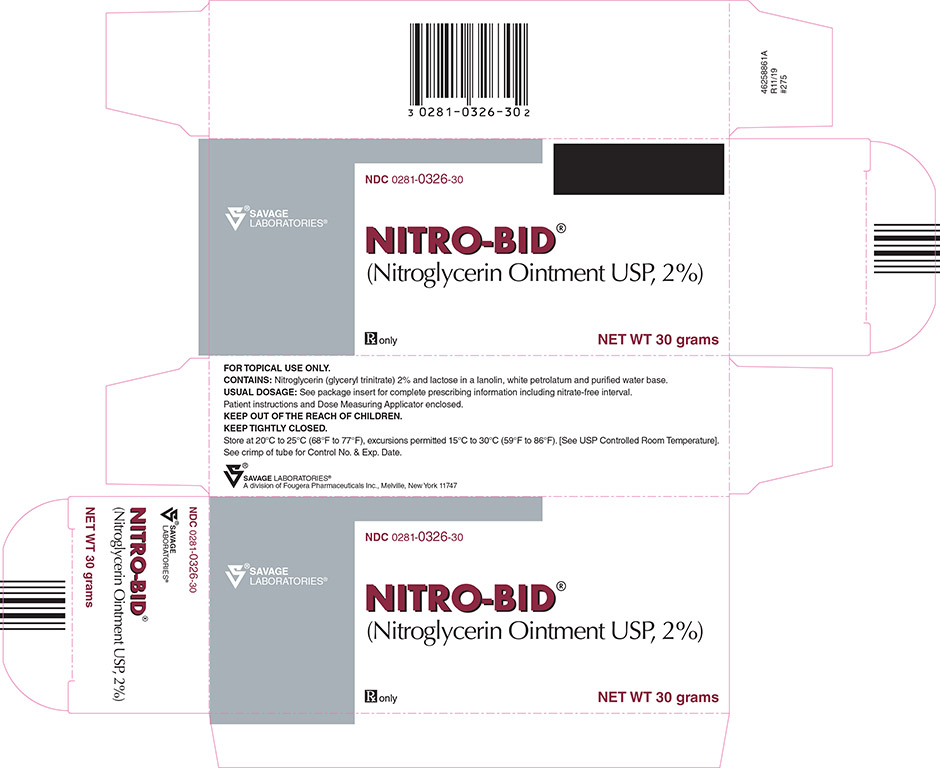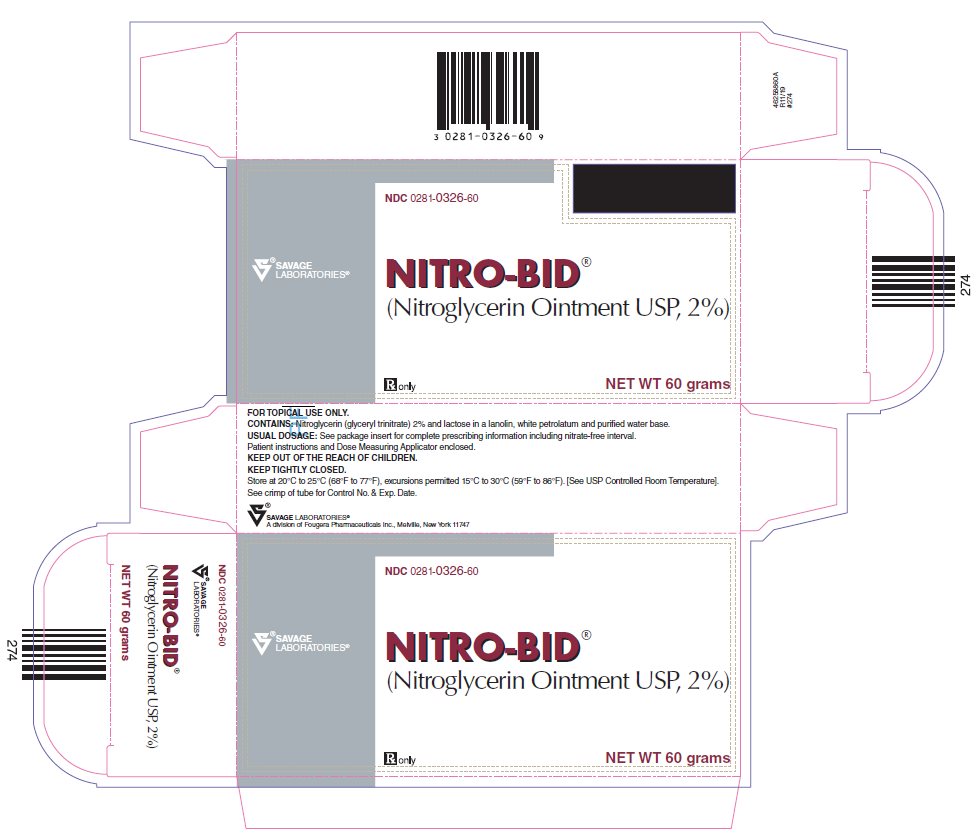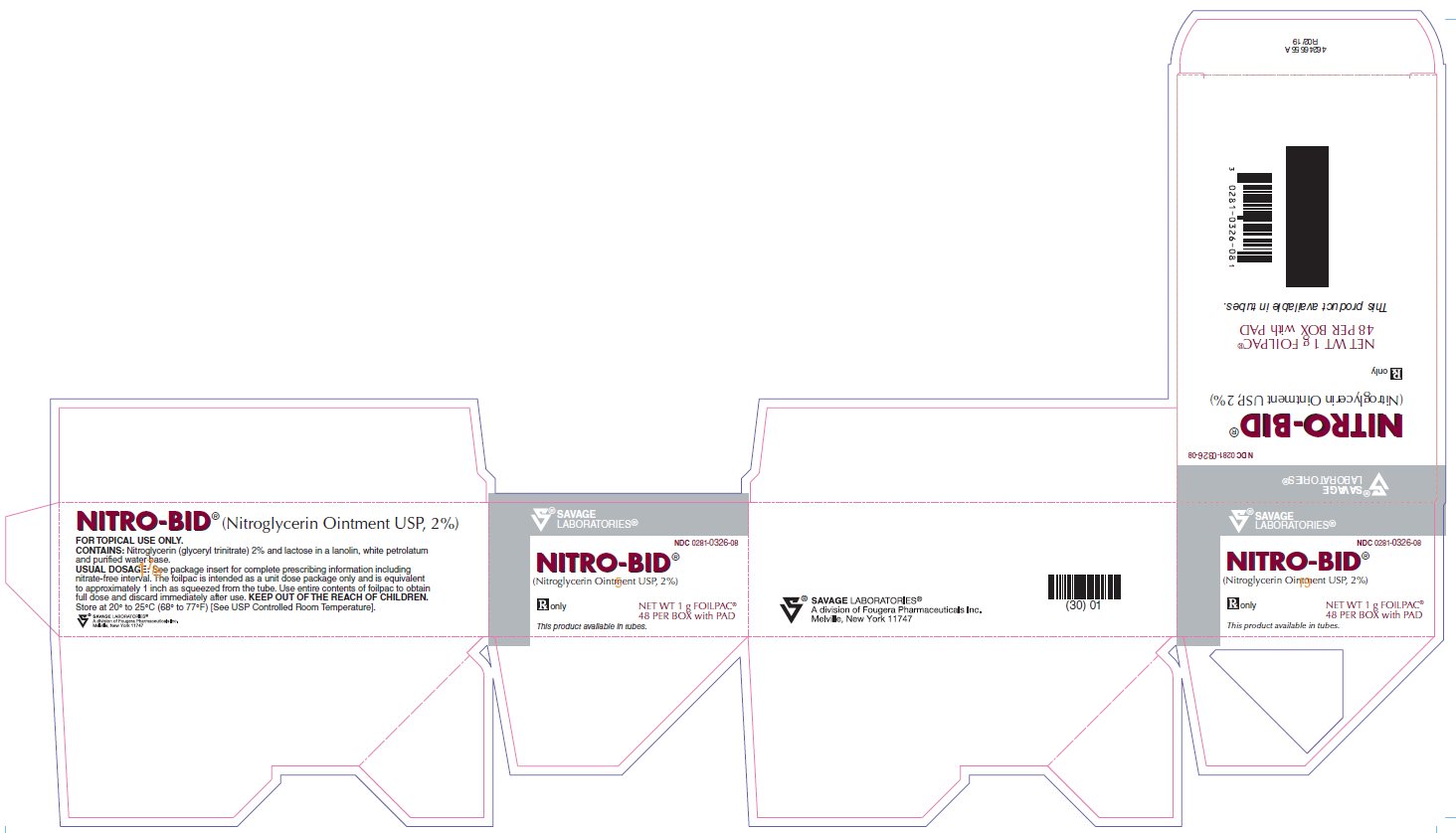 DRUG LABEL: NITRO-BID
NDC: 0281-0326 | Form: OINTMENT
Manufacturer: Savage Laboratories a division of Fougera Pharmaceuticals, LLC
Category: prescription | Type: HUMAN PRESCRIPTION DRUG LABEL
Date: 20260128

ACTIVE INGREDIENTS: nitroglycerin 20 mg/1 g
INACTIVE INGREDIENTS: LACTOSE, UNSPECIFIED FORM; water; petrolatum; LANOLIN

NITRO-BID®
(Nitroglycerin Ointment USP, 2%)

FOR TOPICAL USE ONLY

Rx Only

DESCRIPTION:

Nitroglycerin is 1,2,3-propanetriol trinitrate, an organic nitrate whose structural formula is:

and whose molecular weight is 227.09. The organic nitrates are vasodilators, active on both arteries and veins.

NITRO-BID® for topical use contains lactose and 2% nitroglycerin in a base of lanolin, white petrolatum and purified water. Each inch (2.5 cm), as squeezed from the tube, contains approximately 15 mg of nitroglycerin.

CLINICAL PHARMACOLOGY:

The principal pharmacological action of nitroglycerin is relaxation of vascular smooth muscle and consequent dilatation of peripheral arteries and veins, especially the latter. Dilatation of the veins promotes peripheral pooling of blood and decreases venous return to the heart, thereby reducing left ventricular end-diastolic pressure and pulmonary capillary wedge pressure (preload). Arteriolar relaxation reduces systemic vascular resistance, systolic arterial pressure, and mean arterial pressure (afterload). Dilatation of the coronary arteries also occurs. The relative importance of preload reduction, afterload reduction, and coronary dilatation remains undefined.

Dosing regimens for most chronically used drugs are designed to provide plasma concentrations that are continuously greater than a minimally effective concentration. This strategy is inappropriate for organic nitrates. Several well-controlled clinical trials have used exercise testing to assess the anti-anginal efficacy of continuously-delivered nitrates. In the large majority of these trials, active agents were indistinguishable from placebo after 24 hours (or less) of continuous therapy. Attempts to overcome nitrate tolerance by dose escalation, even to doses far in excess of those used acutely, have consistently failed. Only after nitrates had been absent from the body for several hours was their anti-anginal efficacy restored.

Pharmacokinetics: The volume of distribution of nitroglycerin is about 3 L/kg, and nitroglycerin is cleared from this volume at extremely rapid rates, with a resulting serum half-life of about three minutes. The observed clearance rates (close to 1 L/kg/min) greatly exceed hepatic blood flow; known sites of extrahepatic metabolism include red blood cells and vascular walls.

The first products in the metabolism of nitroglycerin are inorganic nitrate and the 1,2- and 1,3-dinitroglycerols. The dinitrates are less effective vasodilators than nitroglycerin, but they are longer-lived in the serum, and their net contribution to the overall effect of chronic nitroglycerin regimens is not known. The dinitrates are further metabolized to (non-vasoactive) mononitrates and, ultimately, to glycerol and carbon dioxide.

To avoid development of tolerance to nitroglycerin, drug-free intervals of 10 - 12 hours are known to be sufficient; shorter intervals have not been well studied. In one well-controlled clinical trial, subjects receiving nitroglycerin appeared to exhibit a rebound or withdrawal effect, so that their exercise tolerance at the end of the daily drug-free interval was less than that exhibited by the parallel group receiving placebo.

Reliable assay techniques for plasma nitroglycerin levels have only recently become available, and studies using these techniques to define the pharmacokinetics of nitroglycerin ointment have not been reported. Published studies using older techniques provide results that often differ, in similar experimental settings, by an order of magnitude. The data are consistent, however, in suggesting that nitroglycerin levels rise to steady state within an hour or so of application of ointment, and that after removal of nitroglycerin ointment, levels wane with a half-life of about half an hour.

The onset of action of transdermal nitroglycerin is not sufficiently rapid for this product to be useful in aborting an acute anginal episode.

The maximal achievable daily duration of anti-anginal activity provided by nitroglycerin ointment therapy has not been studied. Recent studies of other formulations of nitroglycerin suggest that the maximal achievable daily duration of anti-anginal effect from nitroglycerin ointment will be about 12 hours.

It is reasonable to believe that the rate and extent of nitroglycerin absorption from ointment may vary with the site and square measure of the skin over which a given dose of ointment is spread, but these relationships have not been adequately studied.

CLINICAL STUDIES

Clinical Trials: Controlled trials have demonstrated that nitroglycerin ointment can effectively reduce exercise-related angina for up to 7 hours after a single application. Doses used in clinical trials have ranged from 1/2 inch (1.3 cm; 7.5 mg) to 2 inches (5.1 cm; 30 mg), typically applied to 36 square inches (232 square centimeters) of truncal skin.

In some controlled trials of other organic nitrate formulations, efficacy has declined with time. Because controlled, long-term trials of nitroglycerin ointment have not been reported, it is not known how the efficacy of nitroglycerin ointment may vary during extended therapy.

INDICATIONS AND USAGE:

Nitroglycerin ointment is indicated for the prevention of angina pectoris due to coronary artery disease. The onset of action of transdermal nitroglycerin is not sufficiently rapid for this product to be useful in aborting an acute anginal episode.

CONTRAINDICATIONS:

Allergic reactions to organic nitrates are extremely rare, but they do occur. Nitroglycerin is contraindicated in patients who are allergic to it.

WARNINGS:

Amplification of the vasodilatory effects of nitroglycerin by sildenafil can result in severe hypotension. The time course and dose dependence of this interaction have not been studied. Appropriate supportive care has not been studied, but it seems reasonable to treat this as a nitrate overdose, with elevation of the extremities and with central volume expansion.

The benefits of transdermal nitroglycerin in patients with acute myocardial infarction or congestive heart failure have not been established. If one elects to use nitroglycerin in these conditions, careful clinical or hemodynamic monitoring must be used to avoid the hazards of hypotension and tachycardia.

PRECAUTIONS:

GENERAL PRECAUTIONS

General: Severe hypotension, particularly with upright posture, may occur with even small doses of nitroglycerin. This drug should therefore be used with caution in patients who may be volume depleted or who, for whatever reason, are already hypotensive. Hypotension induced by nitroglycerin may be accompanied by paradoxical bradycardia and increased angina pectoris.

Nitrate therapy may aggravate the angina caused by hypertrophic cardiomyopathy.

As tolerance to other forms of nitroglycerin develops, the effect of sublingual nitroglycerin on exercise tolerance, although still observable, is somewhat blunted. In industrial workers who have had long-term exposure to unknown (presumably high) doses of organic nitrates, tolerance clearly occurs. Chest pains, acute myocardial infarction, and even sudden death have occurred during temporary withdrawal of nitrates from these workers, demonstrating the existence of true physical dependence.

Some clinical trials in angina patients have provided nitroglycerin for about 12 continuous hours of every 24-hour day. During the nitrate-free intervals in some of these trials, anginal attacks have been more easily provoked than before treatment, and patients have demonstrated hemodynamic rebound and decreased exercise tolerance. The importance of these observations to the routine, clinical use of transdermal nitroglycerin is not known.

PATIENT COUNSELING INFORMATION

Information for Patients: Daily headaches sometimes accompany treatment with nitroglycerin. In patients who get these headaches, the headaches are a marker of the activity of the drug. Patients should resist the temptation to avoid headaches by altering the schedule of their treatment with nitroglycerin, since loss of headache is likely to be associated with simultaneous loss of antianginal efficacy.

Treatment with nitroglycerin may be associated with lightheadedness on standing, especially just after rising from a recumbent or seated position. This effect may be more frequent in patients who have also consumed alcohol. Patient instruction leaflet is included.

DRUG INTERACTIONS

Drug Interactions: The vasodilating effects of nitroglycerin may be additive with those of other vasodilators. Alcohol, in particular, has been found to exhibit additive effects of this variety.

Marked symptomatic orthostatic hypotension has been reported when calcium channel blockers and organic nitrates were used in combination. Dose adjustments of either class of agents may be necessary.

CARCINOGENESIS AND MUTAGENESIS AND IMPAIRMENT OF FERTILITY

Carcinogenesis, Mutagenesis, and Impairment of Fertility: Studies to evaluate the carcinogenic or mutagenic potential of nitroglycerin have not been performed. Nitroglycerin's effect upon reproductive capacity is similarly unknown.

PREGNANCY

Pregnancy Category C: Animal reproduction studies have not been conducted with nitroglycerin. It is also not known whether nitroglycerin can cause fetal harm when administered to a pregnant woman or whether it can affect reproductive capacity. Nitroglycerin should be given to a pregnant woman only if clearly needed.

NURSING MOTHERS

Nursing Mothers: It is not known whether nitroglycerin is excreted in human milk. Because many drugs are excreted in human milk, caution should be exercised when nitroglycerin is administered to a nursing woman.

PEDIATRIC USE

Pediatric Use: Safety and effectiveness in pediatric patients have not been established.

ADVERSE REACTIONS:

Adverse reactions to nitroglycerin are generally dose-related, and almost all of these reactions are the result of nitroglycerin's activity as a vasodilator. Headache, which may be severe, is the most commonly reported side effect. Headache may be recurrent with each daily dose, especially at higher doses. Transient episodes of lightheadedness, occasionally related to blood pressure changes, may also occur. Hypotension occurs infrequently, but in some patients it may be severe enough to warrant discontinuation of therapy. Syncope, crescendo angina, and rebound hypertension have been reported but are uncommon.

Allergic reactions to nitroglycerin are also uncommon, and the great majority of those reported have been cases of contact dermatitis or fixed drug eruptions in patients receiving nitroglycerin in ointments or patches. There have been a few reports of genuine anaphylactoid reactions, and these reactions can probably occur in patients receiving nitroglycerin by any route.

Extremely rarely, ordinary doses of organic nitrates have caused methemoglobinemia in normal-seeming patients; for further discussion of its diagnosis and treatment see OVERDOSAGE.

Data are not available to allow estimation of the frequency of adverse reactions during treatment with nitroglycerin ointment.

OVERDOSAGE:

Hemodynamic Effects: The ill effects of nitroglycerin overdose are generally the results of nitroglycerin's capacity to induce vasodilation, venous pooling, reduced cardiac output, and hypotension. These hemodynamic changes may have protean manifestations, including increased intracranial pressure, with any or all of persistent throbbing headache, confusion, and moderate fever; vertigo; palpitations; visual disturbances; nausea and vomiting (possibly with colic and even bloody diarrhea); syncope (especially in the upright posture); air hunger and dyspnea, later followed by reduced ventilatory effort; diaphoresis, with the skin either flushed or cold and clammy; heart block and bradycardia; paralysis; coma; seizures; and death.

Laboratory determinations of serum levels of nitroglycerin and its metabolites are not widely available, and such determinations have, in any event, no established role in the management of nitroglycerin overdose.

No data are available to suggest physiological maneuvers (e.g., maneuvers to change the pH of the urine) that might accelerate elimination of nitroglycerin and its active metabolites. Similarly, it is not known which—if any—of these substances can usefully be removed from the body by hemodialysis.

No specific antagonist to the vasodilator effects of nitroglycerin is known, and no intervention has been subject to controlled study as a therapy of nitroglycerin overdose. Because the hypotension associated with nitroglycerin overdose is the result of venodilatation and arterial hypovolemia, prudent therapy in this situation should be directed toward increase in central fluid volume. Passive elevation of the patient's legs may be sufficient, but intravenous infusion of normal saline or similar fluid may also be necessary.

The use of epinephrine or the arterial vasoconstrictors in this setting is likely to do more harm than good.

In patients with renal disease or congestive heart failure, therapy resulting in central volume expansion is not without hazard. Treatment of nitroglycerin overdose in these patients may be subtle and difficult, and invasive monitoring may be required.

Methemoglobinemia: Nitrate ions liberated during metabolism of nitroglycerin can oxidize hemoglobin into methemoglobin. Even in patients totally without cytochrome b5 reductase activity, however, and even assuming that the nitrate moieties of nitroglycerin are quantitatively applied to oxidation of hemoglobin, about 1 mg/kg of nitroglycerin should be required before any of these patients manifests clinically significant (≥ 10%) methemoglobinemia. In patients with normal reductase function, significant production of methemoglobin should require even larger doses of nitroglycerin. In one study in which 36 patients received 2 to 4 weeks of continuous nitroglycerin therapy at 3.1 to 4.4 mg/hr, the average methemoglobin level measured was 0.2%; this was comparable to that observed in parallel patients who received placebo.

Notwithstanding these observations, there are case reports of significant methemoglobinemia in association with moderate overdoses of organic nitrates. None of the affected patients had been thought to be unusually susceptible.

Methemoglobin levels are available from most clinical laboratories. The diagnosis should be suspected in patients who exhibit signs of impaired oxygen delivery despite adequate cardiac output and adequate arterial pO2. Classically, methemoglobinemic blood is described as chocolate brown, without color change on exposure to air.

When methemoglobinemia is diagnosed, the treatment of choice is methylene blue, 1-2 mg/kg intravenously.

DOSAGE AND ADMINISTRATION:

As noted above (CLINICAL PHARMACOLOGY), controlled trials have demonstrated that nitroglycerin ointment can effectively reduce exercise-related angina for up to 7 hours after a single application. Doses used in clinical trials have ranged from 1/2 inch (1.3 cm; 7.5 mg) to 2 inches (5.1 cm; 30 mg), typically applied to 36 square inches (232 square centimeters) of truncal skin.

It is reasonable to believe that the rate and extent of nitroglycerin absorption from ointment may vary with the site and square measure of the skin over which a given dose of ointment is spread, but these relationships have not been adequately studied.

Controlled trials with other formulations of nitroglycerin have demonstrated that if plasma levels are maintained continuously, all anti-anginal efficacy is lost within 24 hours. This tolerance cannot be overcome by increasing the dose of nitroglycerin. As a result, any regimen of NITRO-BID® administration should include a daily nitrate-free interval. The minimum necessary length of such an interval has not been defined, but studies with other nitroglycerin formulations have shown that 10 to 12 hours is sufficient.

Thus, one appropriate dosing schedule for NITRO-BID® would begin with two daily 1/2- inch (7.5 mg) doses, one applied on rising in the morning and one applied six hours later. The dose could be doubled, and even doubled again, in patients tolerating this dose but failing to respond to it. The foilpac is intended as a unit dose package only and is equivalent to approximately 1 inch as squeezed from the tube. Use entire contents of foilpac to obtain full dose and discard immediately after use.

Each tube of ointment and each box of foilpacs is supplied with a pad of ruled, impermeable, paper applicators. These applicators allow ointment to be absorbed through a much smaller area of skin than that used in any of the reported clinical trials, and the significance of this difference is not known. To apply the ointment using one of the applicators, place the applicator on a flat surface, printed side down. Squeeze the necessary amount of ointment from the tube onto the applicator, place the applicator (ointment side down) on the desired area of the skin, and tape the applicator into place.

HOW SUPPLIED

NITRO-BID® (Nitroglycerin Ointment USP, 2%), is a pale yellow ointment. (Package includes a supply of ruled applicators for convenient application.)

NDC 0281-0326-08 |  | foilpac® Box of 48 x 1 gram
NDC 0281-0326-30 |  | 30 gram tubes
NDC 0281-0326-60 |  | 60 gram tubes

Close tightly, immediately after each use.

Store at 20°-25°C (68°-77°F) [See USP Controlled Room Temperature].

NITRO-BID®(Nitroglycerin Ointment USP, 2%)

SAVAGE LABORATORIES®
A division of Fougera Pharmaceuticals Inc.
Melville, New York 11747

I7326A/IF7326A
R09/11
#274

PATIENT INSTRUCTIONS FOR APPLICATIONS

1. Measure desired dosage of Nitroglycerin Ointment 2% by means of the dose measuring applicator supplied with the tube. Place the applicator on a flat surface, printed side down. Squeeze the necessary amount of ointment from the tube onto the applicator, and place the applicator (ointment side down) on the desired area of the skin.
2. Spread the ointment using the dose measuring applicator lightly onto the chest or other areas of skin if preferred. Do not rub into the skin. Coverage of an area approximately the size of the dose measuring applicator (3 ^1/2′′ by 2 ^1/4′′) should be sufficient to obtain the desired clinical effects. A larger area may be used.
3. Tape the applicator into place.

NOTE: NITRO-BID® can stain clothing. Care should be taken to completely cover the dose measuring applicator with a plastic kitchen wrap.

Dosage Instructions: Dosage instructions should be obtained from your physician. One appropriate dosing schedule for NITRO-BID® would begin with two daily ^1/2 inch (7.5 mg) doses, one applied on rising in the morning and one applied six hours later. The dose could be doubled, and even doubled again, in patients tolerating this dose but failing to respond to it. The foilpac is intended as a unit dose package only and is equivalent to approximately 1 inch as squeezed from the tube. Use entire contents of foilpac to obtain full dose and discard immediately after use.

INFORMATION FOR PATIENTS: Your daily regimen of NITRO-BID® administration should include a nitrate-free period. Studies have shown 10-12 hours is sufficient. The most common side effect which is encountered is headache. Faintness, flushing and dizziness may occur, especially when suddenly arising from the recumbent (lying horizontal) position. If these latter symptoms do occur, it may warrant discontinuation of therapy, and your physician should be notified. For changes in dosage and frequency of application consult your physician.

TUBE: KEEP TUBE TIGHTLY CLOSED.

foilpac®: DISCARD IMMEDIATELY AFTER USE.

Store at 20°-25°C (68°-77°F) [See USP Controlled Room Temperature].

SAVAGE LABORATORIES®
A division of Fougera Pharmaceuticals Inc.
Melville, New York 11747
R09/11

30g Carton

NDC 0281-0326-30

NITRO-BID®
(Nitroglycerin Ointment USP, 2%)

Rx only

NET WT 30 grams

SAVAGE LABORATORIES®

60g Carton

NDC 0281-0326-60

NITRO-BID®

(Nitroglycerin Ointment USP, 2%)

Rx only

NET WT 60 grams

SAVAGE LABORATORIES®

Foil Carton

NDC 0281-0326-08

NITRO-BID®

(Nitroglycerin Ointment USP, 2%)

Rx only

NET WT 1 g FOILPAC®

48 PER BOX with PAD

This product available in tubes.

SAVAGE LABORATORIES®